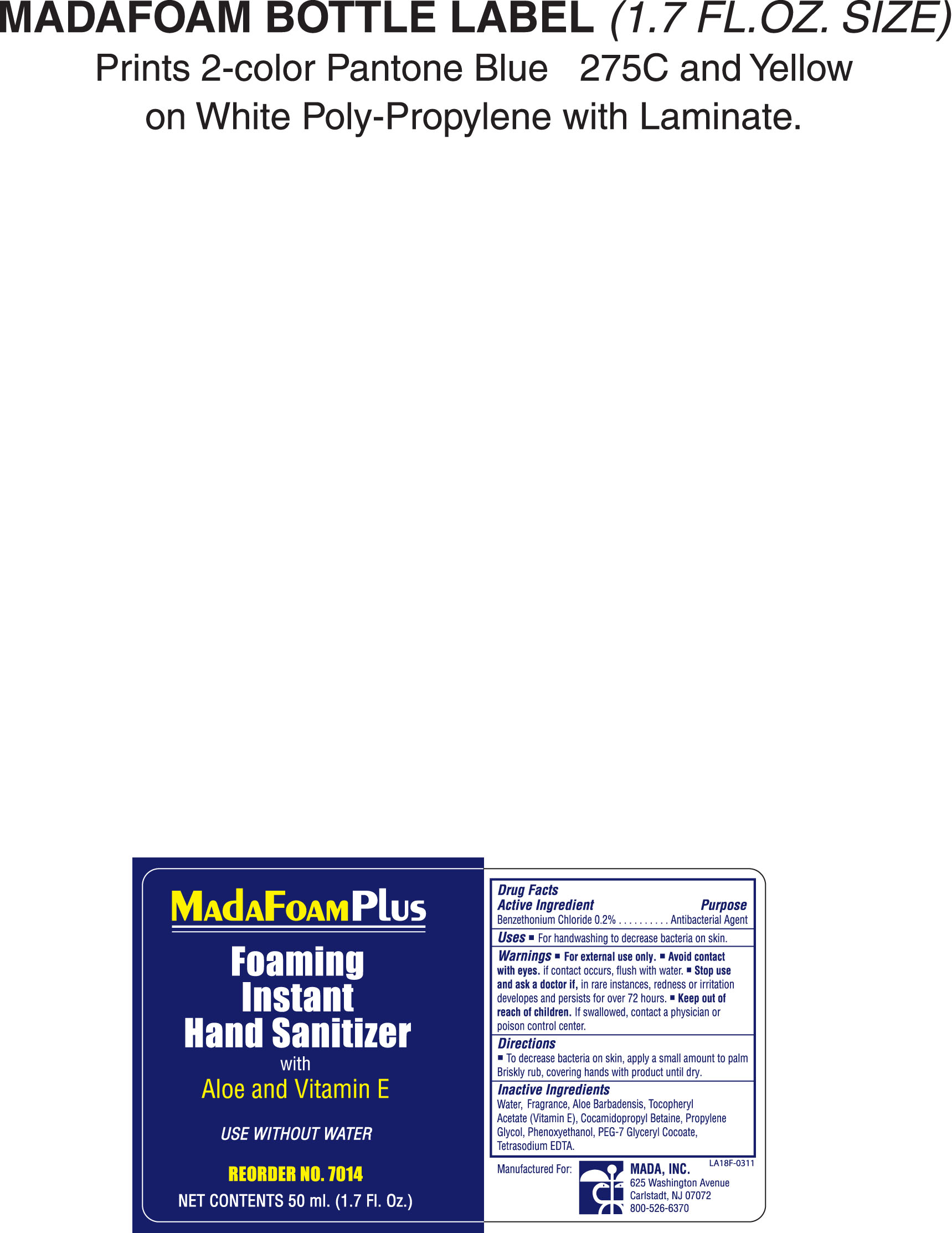 DRUG LABEL: Mada Medical
NDC: 11928-682 | Form: LIQUID
Manufacturer: Mada Medical
Category: otc | Type: HUMAN OTC DRUG LABEL
Date: 20110712

ACTIVE INGREDIENTS: Benzethonium Chloride 0.2 mL/100 mL
INACTIVE INGREDIENTS: Water; Cocamidopropyl Betaine; Edetate Sodium; Propylene Glycol; Phenoxyethanol; Aloe Vera Flower; .ALPHA.-TOCOPHEROL ACETATE, D- ; Glyceryl Cocoate

Drug Facts

ACTIVE INGREDIENT

Benzethonium chloride 0.2 %

PURPOSE

Hand sanitizer to help reduce bacteria on the skin that could cause disease. Recommended for repeated use.

KEEP OUT OF REACH OF CHILDREN

If swallowed, get medical help or contact a poison control center.

INDICATIONS AND USAGE

To decrease bacteria on skin, apply small amount of product to palms. Briskly rub, covering hands with product until dry.

WARNINGS

For external use only. Avoid contact with eyes. If contact occurs, flush with water.

DOSAGE AND ADMINISTRATION

To decrease bacteria on skin, apply small amount to palm. Briskly rub, covering hands with product until dry. Children should be supervised when using product.

INACTIVE INGREDIENT

Water, Fragrance, Aloe Barbadensis, Tocopheryl Acetate, Cocamidopropyl Betaine, PEG-7 Glyceryl Cocoate, Propylene Glycol, Phenoxyethanol, Tetrasodium EDTA

Foaming Instant Hand Sanitizer Bag Label